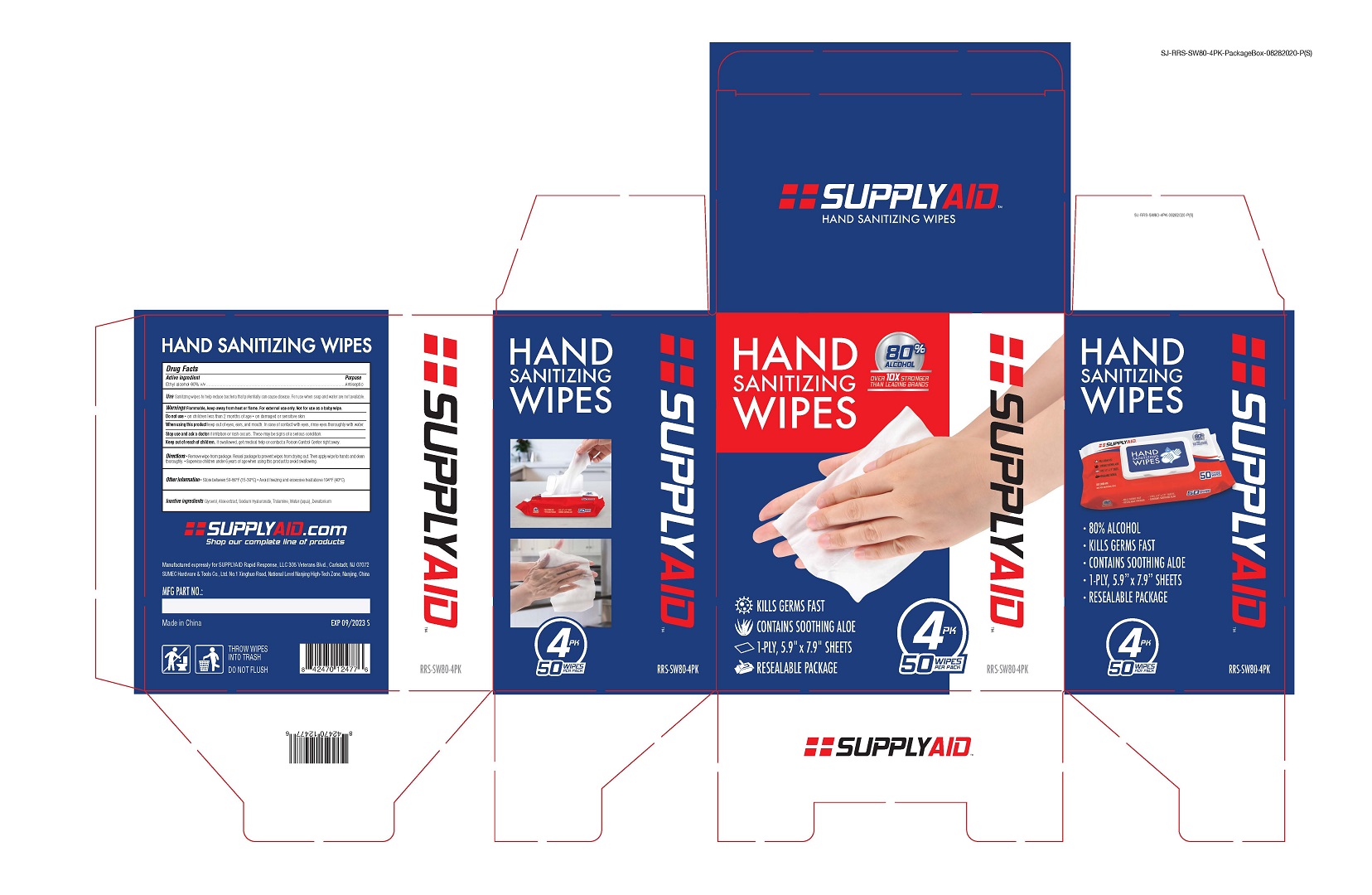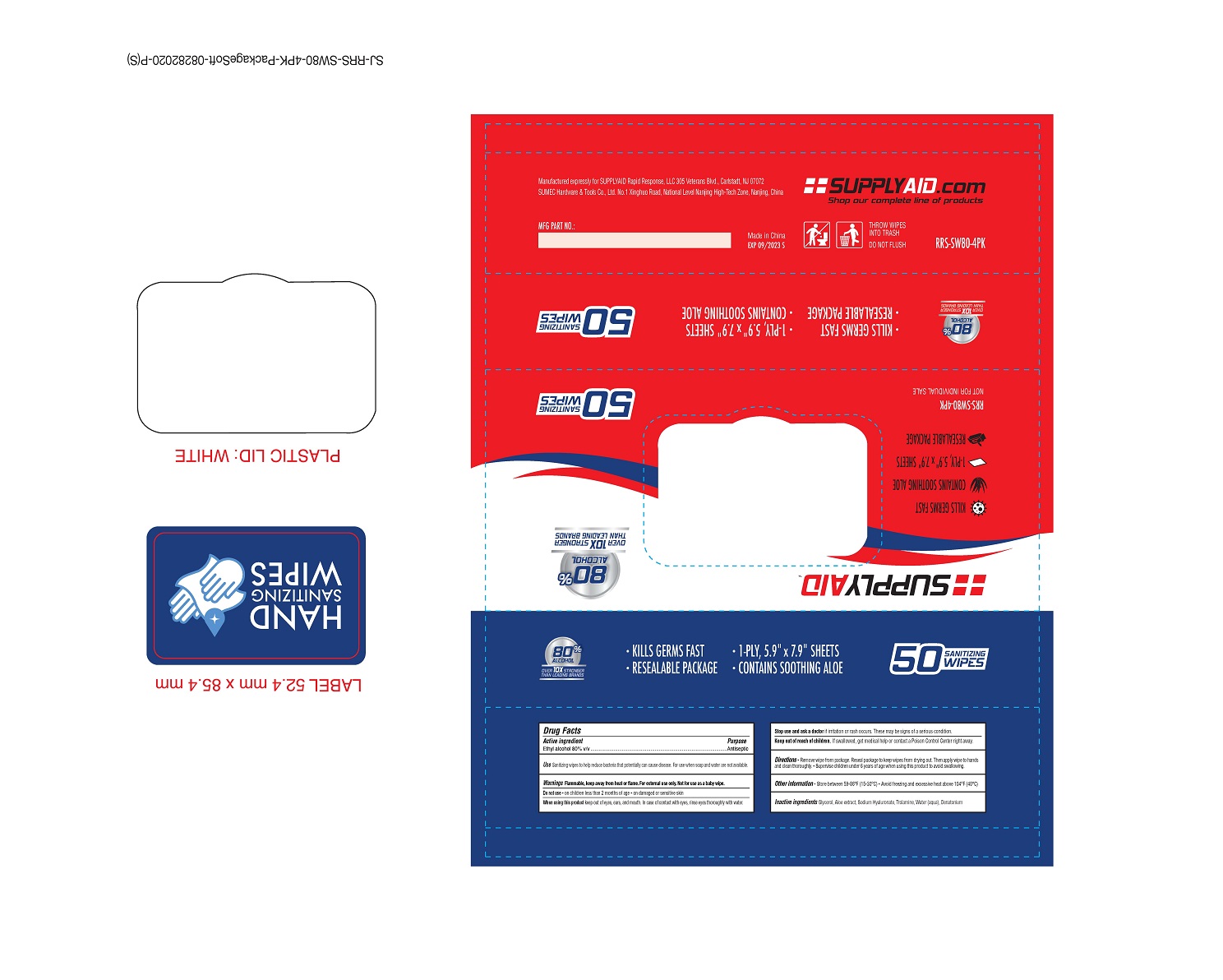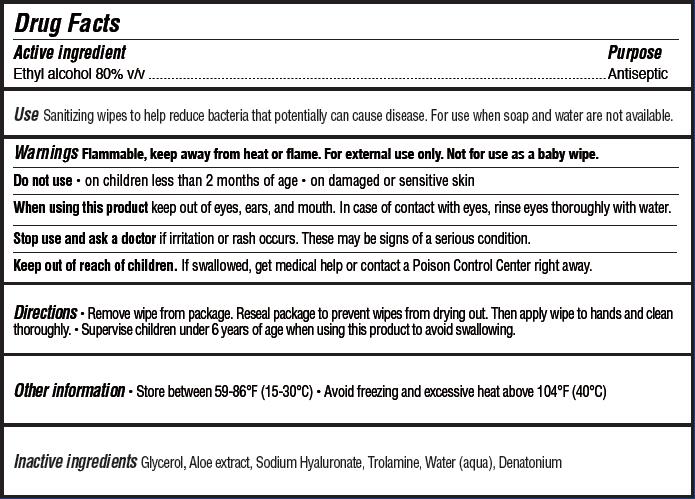 DRUG LABEL: Hand Sanitizing Wipes
NDC: 74035-2051 | Form: CLOTH
Manufacturer: SUMEC Hardware & Tools Co., Ltd.
Category: otc | Type: HUMAN OTC DRUG LABEL
Date: 20200903

ACTIVE INGREDIENTS: ALCOHOL 4.5 mL/1 1
INACTIVE INGREDIENTS: ALOE VERA LEAF; TROLAMINE; WATER; GLYCERIN; HYALURONATE SODIUM; DENATONIUM BENZOATE ANHYDROUS

SUMEC, Wipes, 80% Ethyl alcohol, 50*4

Active Ingredient

Ethyl alcohol 80% v/v. Purpose: Antiseptic

Purpose

Antiseptic

Use

Sanitizing wipes to help reduce bacteria that potentially can cause disease. For use when soap and water are not available.

Warnings

Flammable. Keep away from heat or flame. For external use only. Not for use as a baby wipe.

Do not use

- on children less than 2 months of age
- on damaged or sensitive skin

When using this product keep out of eyes, ears, and mouth.

In case of contact with eyes, rinse eyes thoroughly with water.

Stop use and ask a doctor if irritation or rash occurs. These may be signs of a serious condition.

Keep out of reach of children. If swallowed, get medical help or contact a Poison Control Center right away.

Directions

- Remove wipe from package. Reseal package to prevent wipes from drying out. Then apply wipe to hands and clean thoroughly.
- Supervise children under 6 years of age when using this product to avoid swallowing.

Other information

- Store between 59-86℉ (15-30℃)
- Avoid freezing and excessive heat above 104℉ (40℃)

Inactive ingredients

Glycerol, Aloe extract, Sodium Hyaluronate, Trolamine, Water (aqua), Denatonium